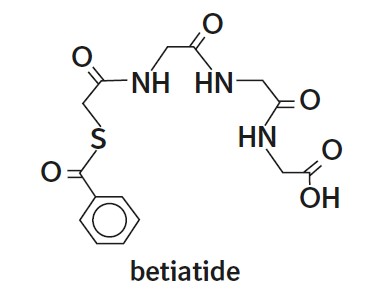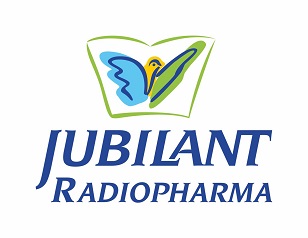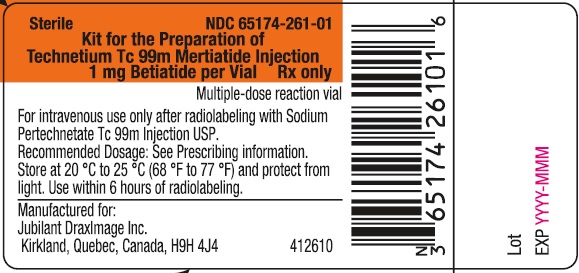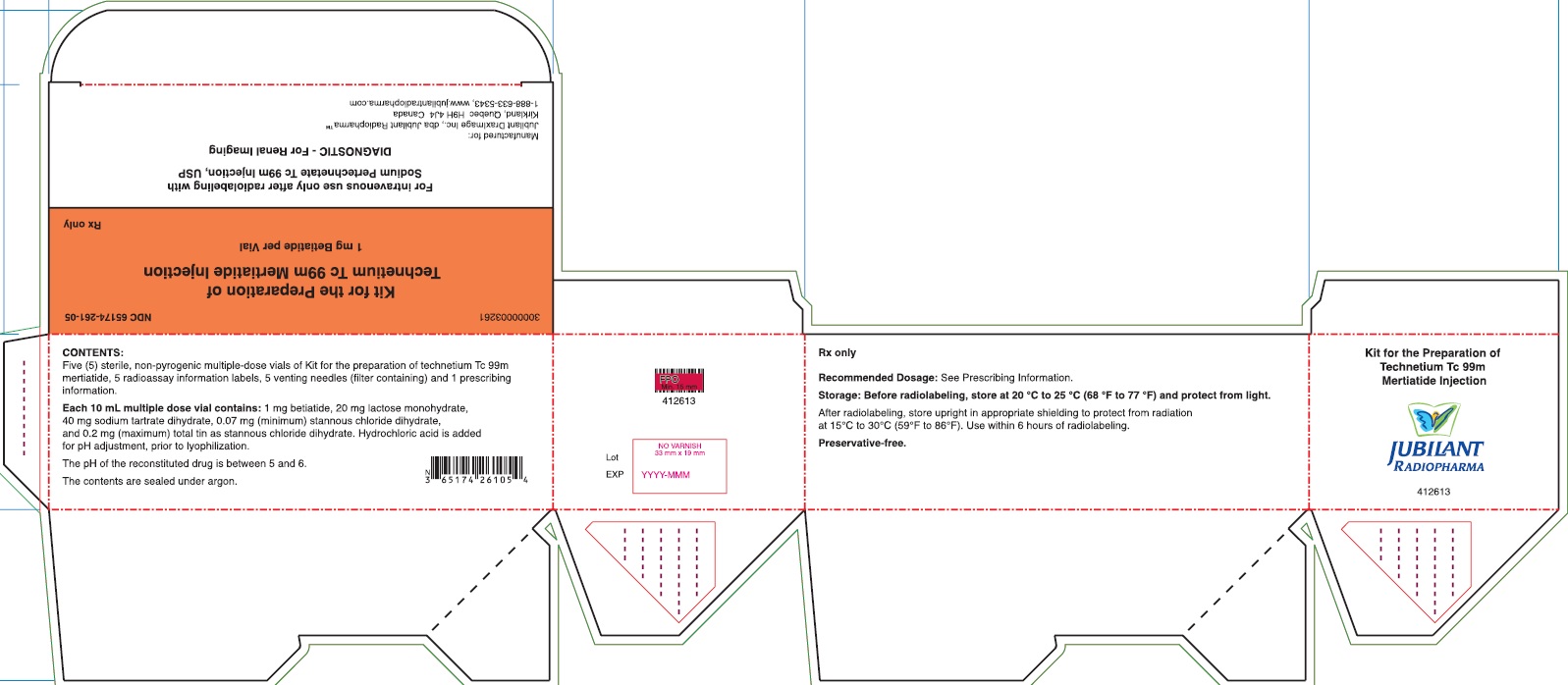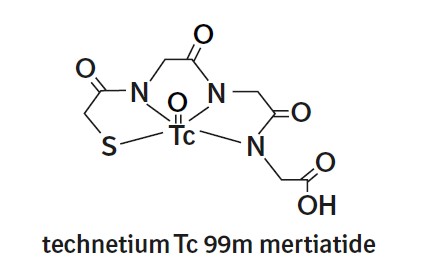 DRUG LABEL: TECHNETIUM Tc 99m MERTIATIDE
NDC: 65174-261 | Form: INJECTION, POWDER, LYOPHILIZED, FOR SOLUTION
Manufacturer: Jubilant DraxImage Inc., dba Jubilant Radiopharma
Category: prescription | Type: HUMAN PRESCRIPTION DRUG LABEL
Date: 20230122

ACTIVE INGREDIENTS: BETIATIDE 1 mg/1 1
INACTIVE INGREDIENTS: STANNOUS CHLORIDE 0.2 mg/1 1; SODIUM TARTRATE DIHYDRATE 40 mg/1 1; LACTOSE MONOHYDRATE 20 mg/1 1; HYDROCHLORIC ACID

HIGHLIGHTS OF PRESCRIBING INFORMATION

These highlights do not include all the information needed to use KIT FOR THE PREPARATION OF TECHNETIUM TC 99M MERTIATIDE safely and effectively. See full prescribing information for Kit for the preparation of Technetium Tc 99m Mertiatide.
KIT FOR THE PREPARATION OF TECHNETIUM TC 99M MERTIATIDE, for intravenous use
Initial U.S. Approval: 1990

1 INDICATIONS AND USAGE

Kit for the Preparation of Technetium Tc 99m Mertiatide Injection, after radiolabeling with technetium-99m, is a radioactive diagnostic agent indicated for use in the diagnosis of congenital and acquired renal abnormalities, renal failure, urinary tract obstruction, and calculi in adults and pediatric patients aged 30 days and older. The product is a diagnostic aid in providing renal function, split function, renal angiograms, and renogram curves for whole kidney and renal cortex. (1)

2 DOSAGE AND ADMINISTRATION

- Instruct patients to drink a sufficient amount of water before administration and continue to drink and to void frequently following administration. (2.2)
- Recommended dose in adult patients:185 MBq to 370 MBq (5 mCi to 10 mCi) as an intravenous bolus injection. (2.3)
- Recommended dose in pediatric patients aged 30 days and older: 2.6 MBq/kg to 5.2 MBq/kg (0.07 mCi/kg to 0.14 mCi/kg) with a minimum dose of 37 MBq (1 mCi) as an intravenous bolus injection. (2.3)
- See Full Prescribing Information for radiation safety, drug preparation, administration, and radiation dosimetry information. (2.1, 2.4, 2.5, 2.6, 2.7)

3 DOSAGE FORMS AND STRENGTHS

Kit for the Preparation of Technetium Tc 99m Mertiatide Injection: 1 mg betiatide as a lyophilized powder in 10 ml glass multiple-dose vial. Upon radiolabeling with technetium-99m, it contains up to 3,700 MBq (100 mCi) technetium Tc 99m mertiatide in approximately 10 mL volume at calibration time.

4 CONTRAINDICATIONS

None. (4)

5 WARNINGS AND PRECAUTIONS

Radiation risks: Ensure safe handling to minimize radiation exposure to patients and healthcare providers. (5.1)

6 ADVERSE REACTIONS

Reported adverse reactions are: tachycardia, nausea, vomiting, shaking chills, fever, seizure, wheezing, dyspnea, itching, rash, and elevation in blood pressure. (6)

To report SUSPECTED ADVERSE REACTIONS, contact Jubilant DraxImage Inc. at 1-888-633-5343 or FDA at 1-800-FDA-1088 or www.fda.gov/medwatch.

8 USE IN SPECIFIC POPULATIONS

Lactation: Temporarily discontinue breastfeeding. A lactating woman should pump and discard breast milk for at least 24 hours after Technetium Tc99m Mertiatide administration. (8.2)

FULL PRESCRIBING INFORMATION

1 INDICATIONS AND USAGE

Kit for the Preparation of Technetium Tc 99m Mertiatide Injection, after radiolabeling with technetium-99m, is indicated for use in the diagnosis of congenital and acquired renal abnormalities, renal failure, urinary tract obstruction, and calculi in adults and pediatric patients aged 30 days and older. The product is a diagnostic aid in providing renal function, split function, renal angiograms, and renogram curves for whole kidney and renal cortex.

2 DOSAGE AND ADMINISTRATION

2.1 Radiation Safety – Drug Handling

After radiolabeling, the kit produces Technetium Tc 99m Mertiatide Injection. Handle Technetium Tc 99m Mertiatide Injection with appropriate safety measures to minimize radiation exposure [see Warnings and Precautions (5.1)]. Use waterproof gloves, effective radiation shielding, and other appropriate safety measures when preparing and handling Technetium Tc 99m Mertiatide Injection.

Radiopharmaceuticals should be used by or under the control of healthcare providers who are qualified by specific training and experience in the safe use and handling of radionuclides, and whose experience and training have been approved by the appropriate governmental agency authorized to license the use of radionuclides.

2.2 Patient Preparation

Instruct patients to drink a sufficient amount of water to ensure adequate hydration prior to administration of Technetium Tc 99m Mertiatide Injection and to continue to drink and void frequently following administration to reduce radiation exposure.

2.3 Recommended Dosage

Adult
The recommended dose in adult patients is 185 MBq to 370 MBq (5 mCi to 10 mCi) as an intravenous bolus injection.

Pediatric
The recommended dose in pediatric patients aged 30 days and older is 2.6 MBq/kg to 5.2 MBq/kg (0.07 mCi/kg to 0.14 mCi/kg) of actual body weight with a minimum dose of 37 MBq (1 mCi) as an intravenous bolus injection.

2.4 Drug Preparation and Handling

Procedural Precautions

- Contents of the vials are intended only for use in the preparation of Technetium Tc 99m Mertiatide Injection, and are NOT to be administered directly to the patient.
- Do not use Sodium Pertechnetate Tc 99m Injection USP more than 6 hours after its elution from the generator.
- Use aseptic techniques for all transfers and vial stopper entries.
- Wear waterproof gloves during the procedure, particularly during the heating of the sample with boiling water.
- Use suitable shielding to reduce radiation exposure. Use one lead shield for incubation with a water bath and another lead shield for dispensing as described in the Procedure for the Preparation of Technetium Tc 99m Mertiatide Injection section below. Make all transfers of sodium pertechnetate Tc 99m solution during the preparation procedure with an adequately shielded syringe.

Procedure for the Preparation of Technetium Tc 99m Mertiatide Injection

1. Prepare a rolling boil water bath containing a lead incubation vial shield with openings cut in it to allow the water to circulate through the shield. Orient the openings of the lead incubation shield to prevent radiation leakage.
  Note: The vial should be in direct contact with the rolling boil water of the bath, and the level of the bath must be at least even with the level of the contents of the vial.
2. Ensure the temperature of the water bath used for heating the reaction vial is at boiling temperature and the temperature of the lead incubation vial shield is equilibrated to the temperature of the water bath before proceeding with the preparation procedure below.
3. Place the reaction vial in a lead dispensing shield fitted with a lid and with a minimum wall thickness of 0.32 cm.
4. Swab the rubber stopper of the reaction vial with an appropriate antiseptic wipe. Insert a filter-containing venting needle (provided) through the vial stopper.
5. Add 4 mL to 10 mL of Sodium Pertechnetate Tc 99m Injection USP containing 740 MBq to 3,700 MBq (20 mCi to 100 mCi) into the vial using a sterile syringe. If necessary, dilute the Sodium Pertechnetate Tc 99m Injection USP with 0.9% Sodium Chloride Injection USP to the desired concentration prior to addition to the vial.
6. Immediately following the addition of Sodium Pertechnetate Tc 99m Injection USP to the reaction vial, withdraw the syringe plunger to a volume of 2 mL, thus removing 2 mL of argon gas, which adds 2 mL of filtered air to the vial to oxidize excess stannous ion and to prevent the formation of technetium-99m labeled impurities.
  Note:The sample vial must be placed in boiling water bath within 5 minutes of the addition of Sodium Pertechnetate Tc 99m solution.
7. Remove both needles from the vial.
8. Invert the reaction vial several times to obtain complete mixing, prior to heating.
9. Immediately transfer the reaction vial to the water bath. Place it inside the lead incubation shield which has been equilibrated to the temperature of the boiling water bath. The reaction vial should be in direct contact with the rolling boil water of the bath, and the level of the water must be at least even with the level of the contents of the vial. Incubate the reaction vial for 10 minutes.
10. Remove the reaction vial from the boiling water bath and place it in the lead dispensing shield. Allow the contents of the vial to cool for approximately 15 minutes.
11. Using proper shielding, visually inspect the vial contents. The solution should be clear and free of particulate matter. If not, do not use the preparation.
12. Assay the reaction vial using a suitable radioactivity calibration system. Record the date, time, total activity, volume, and concentration on the radioassay information label and affix the label to the lead dispensing shield.
13. Test the radiochemical purity of the prepared Technetium Tc 99m Mertiatide Injection according to the recommended method [see Dosage and Administration (2.5)]. If the radiochemical purity is less than 90%, do not use the product.
14. Test the radiochemical impurities of the prepared Technetium Tc 99m Mertiatide Injection according to the recommended method [see Dosage and Administration (2.5)]. If the sum of the hydrophilic impurities and non-elutable impurities is more than 10%, do not use the product.
15. Use the Technetium Tc 99m Mertiatide Injection within 6 hours of radiolabeling and store it at room temperature 15°C to 30°C (59°F to 86°F) until use.
16. Handle and dispose unused radioactive material in accordance with applicable regulations.

2.5 Determination of Radiochemical Purity of Technetium Tc 99m Mertiatide Injection

Required Materials

- Waters Sep-Pak™ C18 Cartridges, Part #51910
- 200 proof ethanol
- 0.9% Sodium Chloride Injection, USP
- 0.001N hydrochloric acid (May be prepared by diluting 1 mL of 0.1N hydrochloric acid to 100 mL with Water for Injection, USP, or by other dilution of more concentrated hydrochloric acid. For example, 0.1 mL of 36% (~11.6N) hydrochloric acid diluted to a total volume of 1,150 mL)
- 1:1 ethanol: 0.9% Sodium Chloride Injection, USP (Prepared by mixing equal volumes of 200 proof ethanol and 0.9% Sodium Chloride Injection, USP)
- 10 mL disposable syringe, no needle required
- 1 mL disposable syringe, with needle
- Disposable culture tubes or vials, minimum 15 mL capacity
- Ion chamber for measurement of radioactive samples

Preparation of Sep-Pak Cartridge

1. Using a 10 mL syringe, push 10 mL of 200 proof ethanol through the Sep-Pak cartridge. Discard the eluate.
2. Flush the cartridge with 10 mL of the 0.001N hydrochloric acid. Discard the eluate.
3. Drain the cartridge by pushing 5 mL of air through the cartridge with the syringe. Discard the eluate.

Sample Analysis

1. Apply 0.1 mL of the Technetium Tc 99m Mertiatide Injection preparation to the head of the cartridge through the longer end of the cartridge using a 1 mL syringe with needle.
  Note: The cartridge and all solutions eluted from it will be radioactive after this step, therefore, use lead dispensing shield to minimize radiation exposure.
2. With a disposable 10 mL syringe, slowly push 10 mL of 0.001N hydrochloric acid through the cartridge. Collect this fraction in a first culture tube or vial for counting.
3. Elute the cartridge with 10 mL of the 1:1 ethanol: 0.9% Sodium Chloride Injection USP solution. Ensure that this solution is pushed through the cartridge slowly so that the elution occurs in a drop-wise manner. Collect this 10 mL fraction in a second culture tube or vial for counting.
4. Place the Sep-Pak cartridge in a third culture tube or vial for counting.

Counting

1. Assay the activity of the first fraction (in 0.001N hydrochloric acid) in an ion chamber. This fraction contains the hydrophilic impurities (free pertechnetate, technetium tartrate, etc.) and a fraction of reduced-hydrolyzed technetium.
2. Assay the activity of the second fraction (in 1:1 ethanol: 0.9% Sodium Chloride Injection, USP). This fraction contains Technetium Tc 99m Mertiatide.
3. Assay the activity of the Sep-Pak cartridge in the third culture tube or vial. This component contains the remaining reduced-hydrolyzed technetium and non-elutable impurities.

Calculations

1. Percent Technetium Tc 99m Mertiatide =
Activity of 2nd (1:1 ethanol: 0.9% Sodium Chloride Injection) fraction x 100%
Total activity of all 3 fractions

Note: Not less than 90% of the activity must be Technetium Tc 99m Mertiatide.

2. Percent hydrophilic impurities =
Activity of 1st (0.001N hydrochloric acid) fraction x 100%
Total activity of all 3 fractions

3. Percent non-elutable impurities =
Activity remaining on Sep-Pak cartridge x 100%
Total activity of all 3 fractions

Note: Total impurities must not be more than 10%.

2.6 Administration Instructions

- Measure the patient dose using a suitable radioactivity calibration system immediately prior to administration.
- Visually inspect the prepared Technetium Tc 99m Mertiatide Injection behind a lead glass shield for particulate matter and discoloration prior to administration. Only use solutions that are clear without visible particles.
- Use aseptic procedures and a shielded syringe to withdraw doses for administration to patients. Wear waterproof gloves during the administration procedure.

2.7 Radiation Dosimetry

The estimated radiation doses per injected activity of Technetium Tc 99m Mertiatide Injection by an intravenous administration are presented in Table 1.

Table 1. Estimated Radiation Equivalent Dose for Intravenously Administered Technetium Tc 99m Mertiatide*

Radiation Equivalent Dose per Unit Activity Administered (mSv/MBq)
Organ | Adult | 15 Years | 10 Years | 5 Years | 1 Year | 8 Days**
Gallbladder Wall | 0.0044 | 0.0053 | 0.007 | 0.011 | 0.034 | 0.073
Lower Large Intestine Wall | 0.0088 | 0.011 | 0.01 | 0.016 | 0.022 | 0.047
Small Intestine | 0.0044 | 0.0055 | 0.0059 | 0.0085 | 0.0075 | 0.014
Upper Large Intestine Wall | 0.0051 | 0.0066 | 0.0086 | 0.013 | 0.013 | 0.026
Kidneys | 0.0039 | 0.0047 | 0.0064 | 0.0093 | 0.015 | 0.038
Liver | 0.00098 | 0.0013 | 0.0018 | 0.0028 | 0.0042 | 0.0087
Ovaries | 0.007 | 0.009 | 0.0065 | 0.0094 | 0.0085 | 0.016
Red Marrow | 0.0013 | 0.0017 | 0.0015 | 0.002 | 0.0022 | 0.0044
Testes | 0.0044 | 0.0064 | 0.005 | 0.0077 | 0.0073 | 0.014
Urinary Bladder Wall | 0.13 | 0.16 | 0.1 | 0.15 | 0.13 | 0.31
Total Body | 0.0018 | 0.0022 | 0.0017 | 0.0026 | 0.003 | 0.0045

*Calculated by Oak Ridge Associated Universities, based upon the pediatric phantom series of Christy and Eckerman of Oak Ridge National Laboratories. The adult radiation absorbed doses were calculated based on data from 10 healthy subjects using the Medical Internal Radiation Dose Committee (MIRD) schema.
** Technetium Tc 99m Mertiatide Injection is not approved for pediatric patients younger than 30 days old [see Indications and Usage (1)].

3 DOSAGE FORMS AND STRENGTHS

Kit for the Preparation of Technetium Tc 99m Mertiatide Injection contains 1 mg betiatide supplied as a white lyophilized powder packaged in 10 mL glass multiple-dose vials. Radiolabeling with sodium pertechnetate Tc 99m injection provides a clear, colorless solution containing up to 3,700 MBq (100 mCi) technetium Tc 99m mertiatide in approximately 10 mL volume at calibration time..

4 CONTRAINDICATIONS

None.

5 WARNINGS AND PRECAUTIONS

5.1 Radiation Risks

Technetium Tc 99m Mertiatide Injection contributes to a patient’s overall long-term cumulative radiation exposure. Long-term cumulative radiation exposure is associated with an increased risk for cancer. Ensure safe handling to minimize radiation exposure to the patient and healthcare providers. Advise patients to hydrate before and after administration and to void frequently after administration [see Dosage and Administration (2.2)].

6 ADVERSE REACTIONS

The following adverse reactions associated with the use of Technetium Tc 99m Mertiatide Injection were identified in clinical studies or postmarketing reports. Because some of these reactions are voluntarily reported from a population of uncertain size, it is not always possible to reliably estimate their frequency or establish a causal relationship to drug exposure.

Cardiac disorders: tachycardia.
Gastrointestinal disorders: nausea, vomiting.
General disorders and administration site conditions: shaking chills, fever.
Nervous system disorders: seizure.
Respiratory, thoracic and mediastinal disorders: wheezing, dyspnea.
Skin and subcutaneous tissue disorders: itching, rash.
Vascular disorders: elevation in blood pressure.

8 USE IN SPECIFIC POPULATIONS

8.1 Pregnancy

Risk Summary

There are no data with technetium Tc 99m mertiatide use in pregnant women to determine a drug-associated risk for major birth defects, miscarriage, or other adverse maternal or fetal outcomes. No animal reproductive studies have been conducted with technetium Tc 99m mertiatide. Although all radiopharmaceuticals have the potential to cause fetal harm depending on the fetal stage of development and the magnitude of the radiation dose, the radiation exposure to the fetus from technetium Tc 99m mertiatide is expected to be low (see Data).

The background risk of major birth defects and miscarriage for the indicated population is unknown. All pregnancies have a background risk of birth defects, loss, or other adverse outcomes. In the U.S. general population, the estimated background risk of major birth defects and miscarriage in clinically recognized pregnancies are 2% to 4% and 15% to 20%, respectively.

Data

Human Data

No adverse fetal effects of radiation risks have been identified for diagnostic procedures involving less than 50 mGy, which represents less than 10 mGy fetal doses.

8.2 Lactation

Risk Summary

There are no data on the presence of technetium Tc 99m mertiatide in breast milk, however, published case reports describe the presence of technetium Tc 99m in breast milk. There are no data on the effects of technetium Tc 99m mertiatide on the breastfed infant or the effects on milk production. Based on clinical guidelines, exposure of technetium Tc 99m mertiatide to a breastfed infant may be minimized by advising a lactating woman to temporarily discontinue breastfeeding and to pump and discard breast milk for a minimum of 24 hours after administration of Technetium Tc 99m Mertiatide Injection. The developmental and health benefits of breastfeeding should be considered along with a mother’s clinical need for Technetium Tc 99m Mertiatide Injection and any potential adverse effects on the breastfed child from technetium Tc 99m mertiatide or from the underlying maternal condition.

8.4 Pediatric Use

Kit for the Preparation of Technetium Tc 99m Mertiatide Injection, after radiolabeling with technetium-99m, is indicated for use in the diagnosis of congenital and acquired renal abnormalities, renal failure, urinary tract obstruction, and calculi in pediatric patients aged 30 days and older.

The safety and effectiveness of Kit for the Preparation of Technetium Tc 99m Mertiatide Injection have not been established in pediatric patients younger than 30 days old.

8.5 Geriatric Use

No formal studies of Technetium Tc 99m Mertiatide Injection in subjects aged 65 and over were performed to determine whether they respond differently than younger adult subjects.

10 OVERDOSAGE

In the event of an overdose of technetium Tc 99m mertiatide, hydration and frequent micturition should be encouraged to minimize the absorbed radiation dose to patient. A diuretic might also be considered. If possible, an estimate of the radiation effective dose given to the patient should be made.

11 DESCRIPTION

11.1 Chemical Characteristics

Kit for the Preparation of Technetium Tc 99m Mertiatide Injection is a sterile, multiple-dose kit for the preparation of technetium Tc 99m mertiatide injection, a radioactive diagnostic agent for intravenous use.

The active ingredient, betiatide, is N-[N-[N-[(benzoylthio) acetyl]glycyl]glycyl]-glycine and has a molecular weight of 367.38 g/mol. After reconstitution with sodium pertechnetate Tc 99m injection, the radioactive agent technetium Tc 99m mertiatide (disodium[N-[N-[N- (mercaptoacetyl) glycyl]glycyl] glycinato (2-) - N,N′,N″,S′]oxotechnetate (2-)) is formed in situ.

Each 10 mL vial contains 1 mg betiatide, 20 mg lactose monohydrate, 40 mg sodium tartrate dihydrate, 0.07 mg (minimum) stannous chloride dihydrate and 0.2 mg (maximum) total tin expressed as stannous chloride dihydrate. Prior to lyophilization, hydrochloric acid is added for pH adjustment. The vial contents are sealed under argon.

After radiolabeling with sodium pertechnetate Tc 99m injection, each vial contains up to 3,700 MBq (100 mCi) of technetium Tc 99m mertiatide in 0.9% sodium chloride injection in approximately 10 mL volume as a sterile, clear, and colorless solution with a pH between 5 and 6.

11.2 Physical Characteristics

Technetium Tc 99m decays by isomeric transition with a physical half-life of 6.02 hours. The principal photon that is useful for detection and imaging is listed in Table 2.

Table 2. Principal Radiation Emission Data
Radiation M | Mean % per Disintegration | Energy (keV)
Gamma-2 | 89.07 | 140.5

To correct for physical decay of the radionuclide, the fractions that remain at selected time intervals after the time of calibration are shown in Table 3.

Table 3. Physical Decay Chart: Technetium Tc 99m, Half-life 6.02 Hours
Hours | Fraction Remaining | Hours | Fraction Remaining
0* | 1.000 | 7 | 0.447
1 | 0.891 | 8 | 0.398
2 | 0.794 | 9 | 0.355
3 | 0.708 | 10 | 0.316
4 | 0.631 | 11 | 0.282
5 | 0.562 | 12 | 0.251
6 | 0.501

* Calibration Time

11.3 External Radiation

The specific gamma ray constant for technetium-99m is 0.78 R/mCi-hr at 1 cm. The first half-value thickness of lead (Pb) for technetium-99m is 0.017 cm. The use of 0.25 cm of Pb, for example, will decrease the external radiation exposure by a factor of about 1,000. Table 4 displays the radiation attenuation by lead shielding.

Table 4. Radiation Attenuation by Lead Shielding
Shield Thickness (Pb) cm | Coefficient of Attenuation
0.017 | 0.5
0.08 | 10^-1
0.16 | 10^-2
0.25 | 10^-3
0.33 | 10^-4

12 CLINICAL PHARMACOLOGY

12.1 Mechanism of Action

Following intravenous administration for renal imaging, Technetium Tc 99m Mertiatide is rapidly cleared from the blood. It is cleared by the kidneys and excreted in the urine.

12.2 Pharmacodynamics

Following intravenous injection of technetium Tc 99m mertiatide, the uptake, concentration, and excretion of the tracer by the kidney can be monitored to assess renal function.

12.3 Pharmacokinetics

Distribution

After an intravenous administration in healthy adult subjects, 89% of technetium Tc 99m mertiatide was plasma-protein bound. The protein binding is reversible.

Elimination

Excretion

In healthy subjects, the plasma clearance was approximately 0.3 liters/minute and the amount of technetium Tc 99m mertiatide excreted in the urine in 3 hours was nearly 90% of the injected dose.

Specific Populations

Patients with Renal Impairment

In a study performed in three patients with renal impairment (serum creatinine greater than 6.3 mg/dL), 78% of the tracer was plasma protein bound after intravenous injection. The mean plasma clearance of technetium Tc 99m mertiatide was 0.03 liters/minute and 21.3% was excreted in 3 hours on average. In both healthy subjects and patients with renal impairment, the plasma concentration-time profile showed a biexponential decline.

13 NONCLINICAL TOXICOLOGY

13.1 Carcinogenesis, Mutagenesis, Impairment of Fertility

No long term animal studies have been performed to evaluate carcinogenic or mutagenic potential, or whether this drug affects fertility in males or females.

16 HOW SUPPLIED/STORAGE AND HANDLING

How Supplied

Kit for the Preparation of Technetium Tc 99m Mertiatide Injection containing 1 mg betiatide, is supplied as a white lyophilized powder packaged in a sterile, multiple-dose 10 mL vial as a carton of 5 vials (NDC 65174-261-05). The carton also contains:

- 5 venting needles with filter.

- 5 radioassay information labels for the radiolabeled product.

The radionuclide is not part of Kit for the Preparation of Technetium Tc 99m Mertiatide Injection.

Storage and Handling

Before radiolabeling, store at controlled room temperature 20°C to 25°C (68°F to 77°F) [see USP Controlled Room Temperature] and protect from light.

After radiolabeling with sodium pertechnetate Tc 99m injection, store vial upright in shielding to protect from radiation at room temperature 15°C to 30°C (59°F to 86°F). Use within 6 hours of radiolabeling.

Dispose of unused Technetium Tc 99m Mertiatide Injection in compliance with the regulations of the government agency authorized to license the use of this radionuclide.

This preparation is approved for use by persons under license by the Nuclear Regulatory Commission or the relevant regulatory authority of an Agreement State.

17 PATIENT COUNSELING INFORMATION

Adequate Hydration

Advise patients to drink sufficient amount of water to ensure adequate hydration before administration of Technetium Tc 99m Mertiatide Injection and to continue to drink and void frequently following administration to minimize radiation dose [see Dosage and Administration (2.2) and Warning and Precautions (5.1)].
Pregnancy:
Advise pregnant women of the risk of fetal exposure to radiation doses if they undergo a radionuclide procedure [see Use in Specific Populations (8.1)].

Lactation:
Advise a lactating woman to temporarily discontinue breastfeeding and to pump and discard breast milk for at least 24 hours after Technetium Tc 99m Mertiatide Injection administration to minimize radiation exposure to a breastfed infant [see Use in Specific Populations (8.2)].

Manufactured for:

Jubilant DraxImage Inc., dba Jubilant Radiopharma™

16 751 TransCanada Highway
Kirkland, Quebec H9H 4J4 Canada
1-888-633-5343
www.jubilantradiopharma.com

Art Rev.: 3.0

Sep-Pak™ is a trademark of Waters Technologies Corporation.
Jubilant Radiopharma™ is a trademark used under license by Jubilant DraxImage Inc.

PACKAGE/LABEL PRINCIPAL DISPLAY PANEL - 5 VIAL BOX

NDC 65174-261-05

Kit for the Preparation of Technetium Tc 99m Mertiatide
1 mg Betiatide per Vial
Rx only

For intravenous use only after radiolabeling with

Sodium Pertechnetate Tc 99m Injection, USP

DIAGNOSTIC - For Renal Imaging

Manufactured for:
Jubilant DraxImage Inc., dba Jubilant Radiopharma™
Kirkland, Quebec H9H 4J4 Canada
1-888-633-5343, www.jubilantradiopharma.com

CONTENTS:
Five (5) sterile, non-pyrogenic multiple-dose vials of Kit for the preparation of technetium Tc 99m mertiatide, 5 radioassay information labels, 5 venting needles (filter containing) and 1 prescribing information.

Each 10 mL multiple dose vial contains: 1 mg betiatide, 20 mg lactose monohydrate, 40 mg tartrate dihydrate, 0.07 (minimum) stannous chloride dihydrate, and 0.2 mg (maximum) total tin as stannous chloride dihydrate. Hydrochloric acid is added for pH adjustment, prior to lyophilization.

The pH of the reconstituted drug is between 5 and 6.

The contents are sealed under argon.

Rx only

Recommended Dosage: See Prescrbing Information.

Storage: Before radiolabeling, store at 20 °C to 25 °C (68 °F to 77 °F) and protect from light.

After radiolabeling, store upright inappropriate shielding to protect from radiation at 15°C to 30°C (59°F to 86°F). Use within 6 hours of radiolabeling.

Preservative-free.

PACKAGE/LABEL PRINCIPAL DISPLAY PANEL - VIAL CONTAINER (10 mL Multi-Dose Reaction Vial)

Sterile NDC 65174-261-01
Kit for the Preparation of Technetium Tc 99m Mertiatide Injection
1 mg Betiatide per Vial Rx only

Multiple-dose reaction vial

For intravenous use only after radiolabeling with Sodium Pertechnetate Tc 99m Injection USP.

Recommended Dosage: See Prescribing information.

Store at 20 °C to 25 °C (68 °F to 77 °F) and protect from light. Use within 6 hours of radiolabeling.

Manufactured for:
Jubilant DraxImage Inc.
Kirkland, Quebec, Canada H9H 4J4